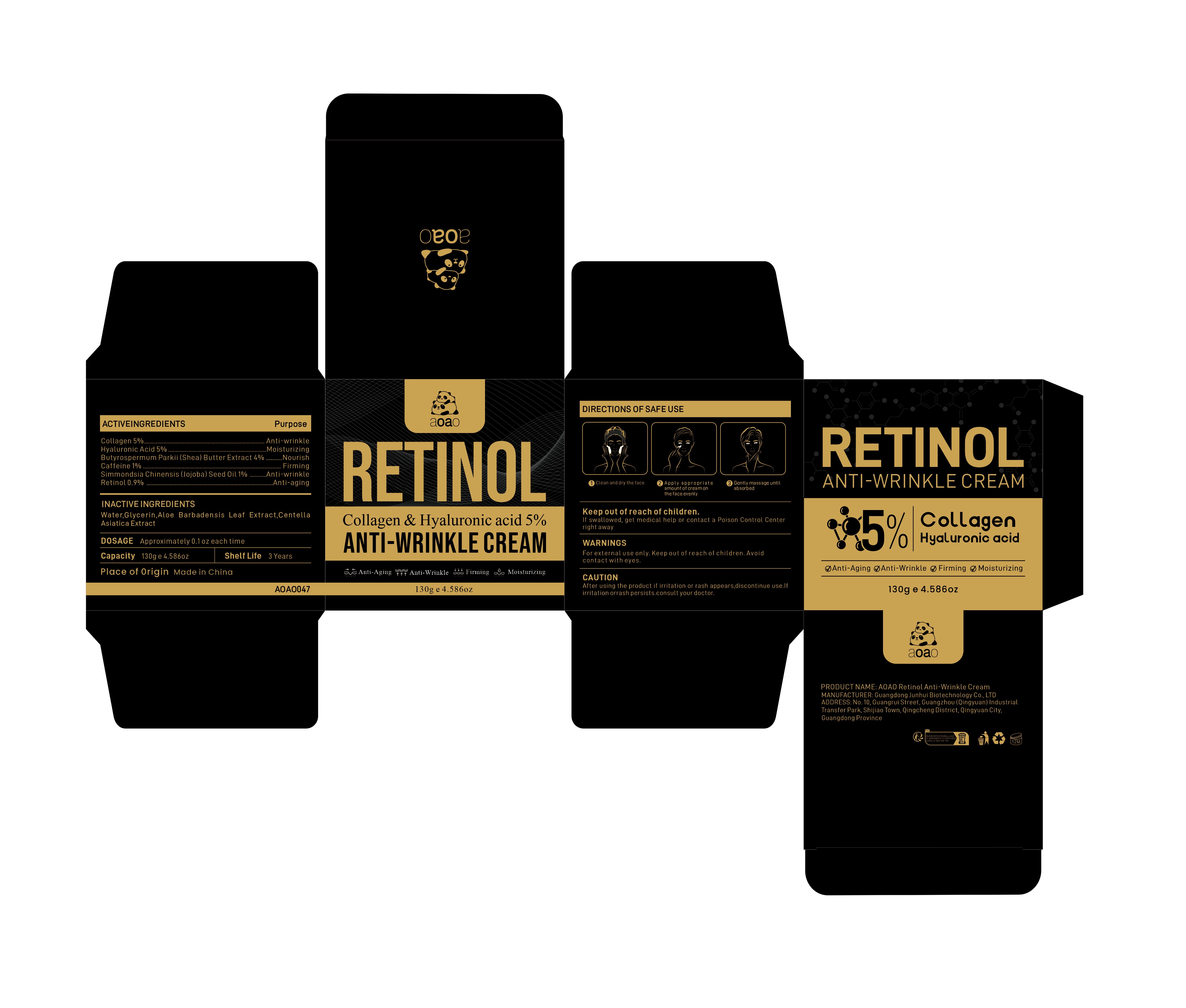 DRUG LABEL: AOAO Retinol Anti-Wrinkle Cream
NDC: 84509-045 | Form: CREAM
Manufacturer: Guangdong Junhui Biotechnology Co., LTD
Category: otc | Type: HUMAN OTC DRUG LABEL
Date: 20241107

ACTIVE INGREDIENTS: COLLAGEN, SOLUBLE, FISH SKIN 6500 mg/130 g; SIMMONDSIA CHINENSIS (JOJOBA) SEED OIL 1300 mg/130 g; RETINOL 1170 mg/130 g; HYALURONIC ACID 6500 mg/130 g; BUTYROSPERMUM PARKII (SHEA) BUTTER EXTRACT 5200 mg/130 g; CAFFEINE 1300 mg/130 g
INACTIVE INGREDIENTS: CENTELLA ASIATICA TRITERPENOIDS; ALOE BARBADENSIS LEAF EXTRACT; GLYCERIN; WATER

Active Ingredients

Collagen 5%
Butyrospermum Parkii (Shea) Butter Extract 4%
Hyaluronic Acid 5%
Caffeine 1%
Simmondsia Chinensis (Jojoba) Seed Oil 1%
Retinol 0.9%

Purpose

Anti-wrinkle
Nourish
Moisturizing
Firming
Anti-aging

Uses

1、Clean and dry the face
2、Apply an appropriateamount of face cream evenly on the face
3、Gently massage until absorbed

Warnings

For external use only. Keep out ofreach of children.Avoid contact with eyes

Keep out of reach of children

If swallowed, get medical help or contact a Poison Control Center right away

CAUTION

After using the product if irritation or rash appears,discontinue use.If irritation or rash persists.consult your doctor.

Inactive Ingredients

Water,Glycerin，Aloe Barbadensis Leaf Extract，Centella Asiatica Extract

Product Name

AOAO Retinol Anti-Wrinkle Cream

DOSAGE

Approximately 0.1oz each time

Manufacturer

Guangdong Junhui Biotechnology Co., LTD

Address

No. 10, Guangrui Street, Guangzhou (Qingyuan) Industrial Transfer Park, Shijiao Town, Qingcheng District, Qingyuan City, Guangdong Province

Capacity

130g e 4.586oz

Shelf Life

3 Years

Place of Origin

Made in China